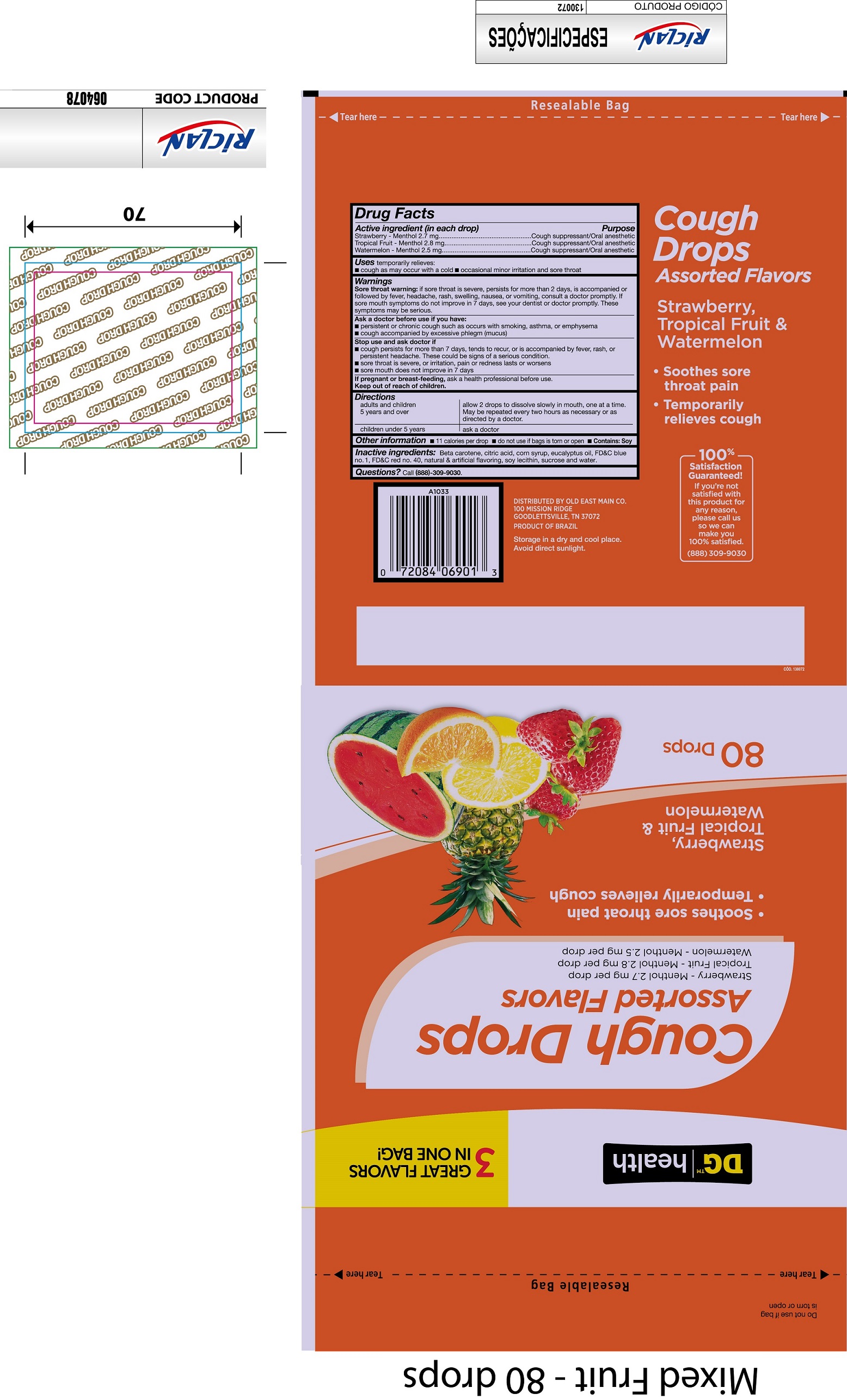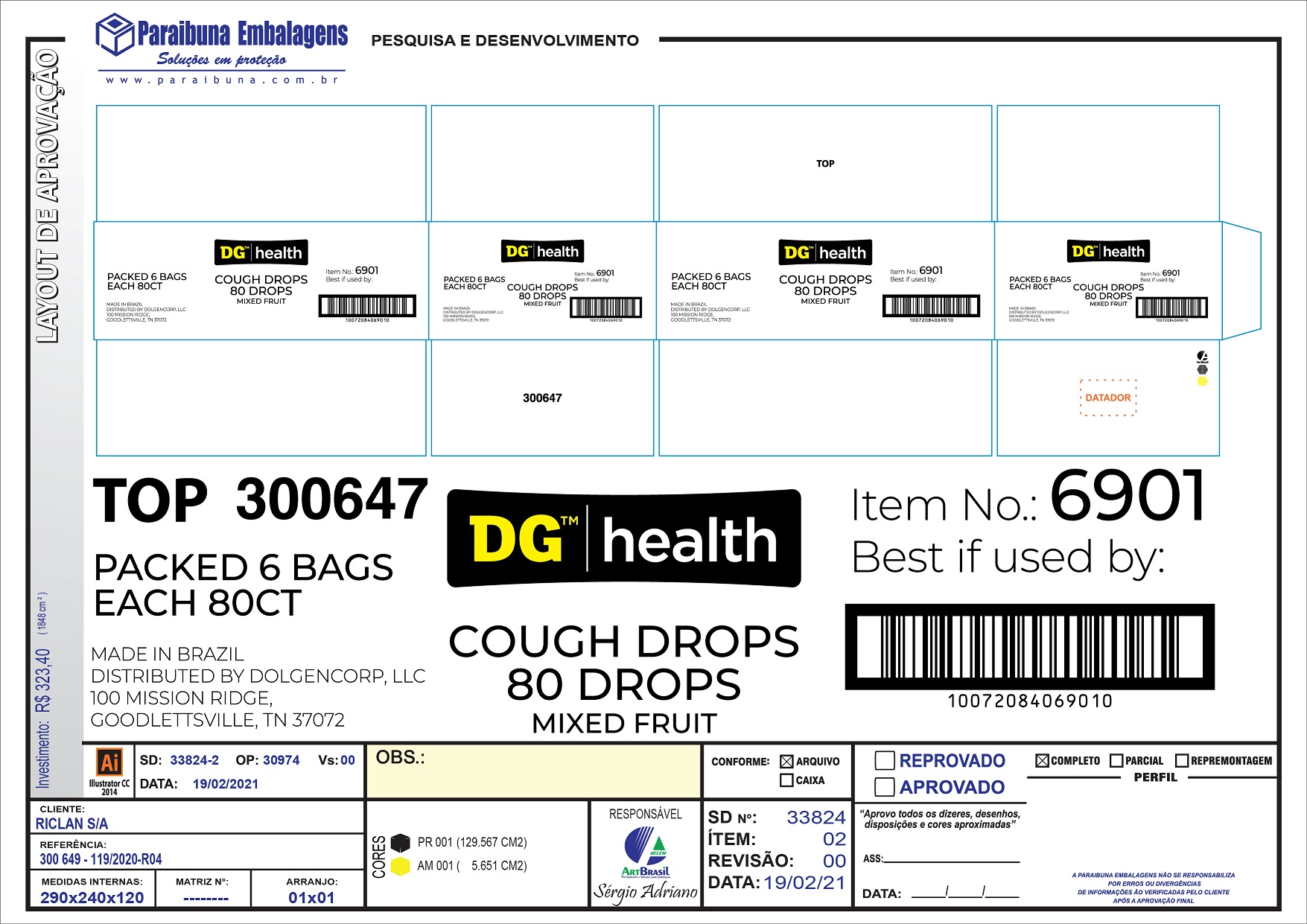 DRUG LABEL: DG Health Cough Drops Assorted Flavors
NDC: 75712-001 | Form: KIT | Route: TOPICAL
Manufacturer: Dollar General Corporation
Category: otc | Type: HUMAN OTC DRUG LABEL
Date: 20231026

ACTIVE INGREDIENTS: MENTHOL 2.7 mg/1 1; MENTHOL 2.8 mg/1 1; MENTHOL 2.8 mg/1 1
INACTIVE INGREDIENTS: BETA CAROTENE; CITRIC ACID MONOHYDRATE; CORN SYRUP; EUCALYPTUS OIL; FD&C BLUE NO. 1; FD&C RED NO. 40; LECITHIN, SOYBEAN; SUCROSE; WATER; BETA CAROTENE; CITRIC ACID MONOHYDRATE; CORN SYRUP; EUCALYPTUS OIL; FD&C BLUE NO. 1; FD&C RED NO. 40; LECITHIN, SOYBEAN; SUCROSE; WATER; BETA CAROTENE; CITRIC ACID MONOHYDRATE; CORN SYRUP; EUCALYPTUS OIL; FD&C BLUE NO. 1; FD&C RED NO. 40; LECITHIN, SOYBEAN; SUCROSE; WATER

DG Health Cough Drops Assorted Flavors

Active ingredient (in each drop)

Strawberry - Menthol 2.7 mg

Tropical Fruit - Menthol 2.8 mg

Watermelon - Menthol 2.5 mg

Purpose

Cough suppressant/Oral anesthetic

Uses

temporarily relieves:

- cough as may occur with a cold
- occasional minor irritation and sore throat

Warnings

if sore throat is severe, persists for more than 2 days, is accompanied or followed by fever, headache, rash, swelling, nausea, or vomiting, consult a doctor promptly. If sore mouth symptoms do not improve in 7 days, see your dentist or doctor promptly. These symptoms may be serious. Sore throat warning:

Ask a doctor before use if you have:

- persistent or chronic cough such as occurs with smoking, asthma, or emphysema
- cough accompanied by excessive phlegm (mucus)

Stop use and ask doctor if

- cough persists for more than 7 days, tends to recur, or is accompanied by fever, rash, or persistent headache, These could be signs of a serious condition.
- sore throat is severe, or irritation, pain or redness lasts or worsens
- sore mouth does not improve in 7 days

If pregnant or breast-feeding,

ask a health professional before use.

Directions

adults and children 5 years and over | allow 2 drops to dissolve slowly in mouth, one at a time. May be repeated every two hours as necessary or as directed by a doctor.
children under 5 years | ask a doctor

Other information

- 11 calories per drop
- do not use if bags is torn or open
- Contains: Soy

Inactive ingredients

Beta carotene, citric acid, corn syrup, eucalyptus oil, FD&C blue no. 1, FD&C red no, 40, natural & artificial flavoring, soy lecithin, sucrose and water.

Questions?

Call (888) 309-9030.